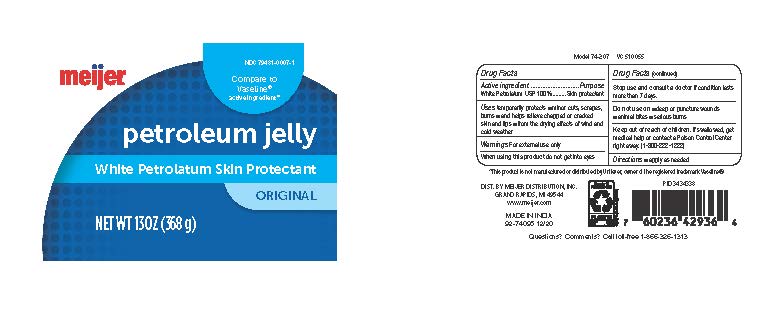 DRUG LABEL: Meijer Petroleum Jelly
NDC: 79481-0007 | Form: JELLY
Manufacturer: Meijer Distribution, Inc
Category: otc | Type: HUMAN OTC DRUG LABEL
Date: 20241218

ACTIVE INGREDIENTS: PETROLATUM 100 g/100 g

Meijer Petroleum jelly

Drug Facts

Active Ingredient

White Petrolatum USP 100%

Purpose

Skin protectant

Uses

temporarily protects ■ minor cuts, scrapes,
burns ■ and help relieve chapped or cracked
skin and lips ■ from the drying effects of wind and
cold weather

Warnings

For external use only

When using this product

do not get into eyes

Stop use and consult a doctor

if the condition lasts more than 7 days.

Do not use on

■ deep or puncture wounds
■ animal bites ■ serious burns

Keep out of reach of children

If swallowed, get medical help or contact a Poison Control Center right away. (1-800-222-1222)

Directions

apply as needed

INACTIVE INGREDIENT

Water